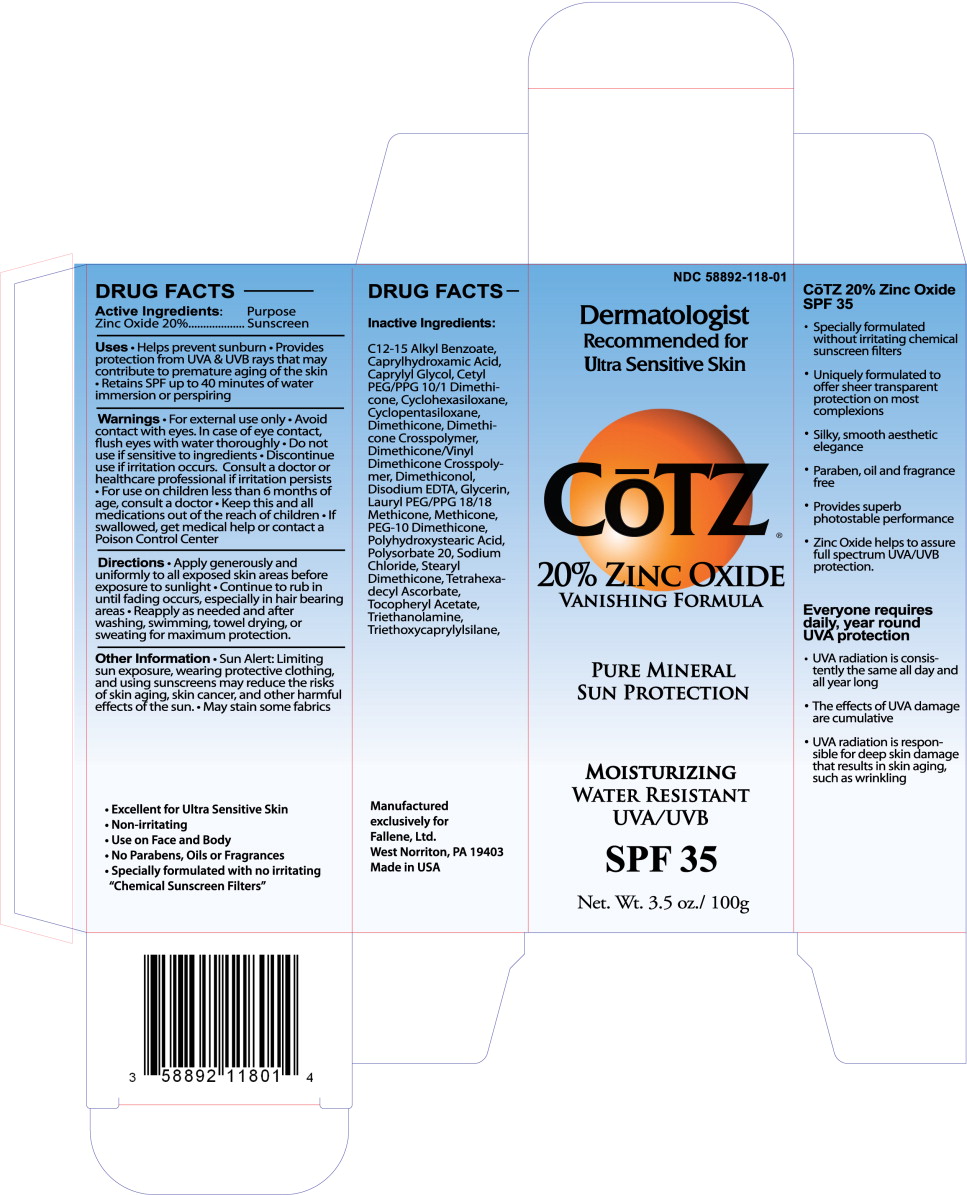 DRUG LABEL: CoTZ SPF 35 
NDC: 58892-118 | Form: LOTION
Manufacturer: Fallien Cosmeceuticals, LTD.
Category: otc | Type: HUMAN OTC DRUG LABEL
Date: 20110607

ACTIVE INGREDIENTS: Zinc Oxide 200 mg/1 g
INACTIVE INGREDIENTS: Alkyl (C12-15) Benzoate; Caprylhydroxamic Acid; Caprylyl Glycol; Cyclomethicone 6; Cyclomethicone 5; Dimethicone; Edetate Disodium; Glycerin; Hydroxystearic Acid; Polysorbate 20; Sodium Chloride; Tetrahexyldecyl Ascorbate; .Alpha.-Tocopherol Acetate, D-; Trolamine; Triethoxycaprylylsilane; Water

CoTZ SPF 35 Sunscreen

Active Ingredients:

Zinc Oxide 20%.

Purpose

Sunscreen

Uses

- Helps prevent sunburn
- Provides protection from UVA & UVB rays that may contribute to premature aging of the skin
- Retains SPF up to 40 minutes of water immersion or perspiring

Warnings

- For external use only
- Avoid contact with eyes. In case of eye contact, flush eyes with water thoroughly
- Do not use if sensitive to ingredients
- Discontinue use if irritation occurs. Consult a doctor or healthcare professional if irritation persists
- For use on children less than 6 months of age, consult a doctor
- Keep this and all medications out of the reach of children
- If swallowed, get medical help or contact a Poison Control Center

Directions

- Apply generously and uniformly to all exposed skin areas before exposure to sunlight
- Continue to rub in until fading occurs, especially in hair bearing areas
- Reapply as needed and after washing, swimming, towel drying, or sweating for maximum protection.

Other Information

- Sun Alert: Limiting sun exposure, wearing protective clothing, and using sunscreens may reduce the risks of skin aging, skin cancer, and other harmful effects of the sun.
- May stain some fabrics

Inactive Ingredients:

C12-15 Alkyl Benzoate, Caprylhydroxamic Acid, Caprylyl Glycol, Cetyl PEG/PPG 10/1 Dimethicone, Cyclohexasiloxane, Cyclopentasiloxane, Dimethicone, Dimethicone Crosspolymer, Dimethicone/VinyI Dimethicone Crosspolymer, Dimethiconol, Disodium EDTA, Glycerin, Lauryl PEG/PPG 18/18 Methicone, Methicone, PEG-10 Dimethicone, Polyhydroxystearic Acid, Polysorbate 20, Sodium Chloride, Stearyl Dimethicone, Tetrahexadecyl Ascorbate, Tocopheryl Acetate, Triethanolamine, Triethoxycaprylylsilane,

Manufactured
exclusively for
Fallene, Ltd.
West Norriton, PA 19403
Made in USA

Principal Display Panel – 3.5oz Carton Label

NDC 58892-118-01

Dermatologist

Recommended for

Ultra Sensitive Skin

CoTZ®

20% Zinc Oxide

vanishing formula

Pure Mineral

Sun protection

Moisturizing

water resistant

uva/uvb

SPF 35

Net. Wt. 3.5 oz./ 100g